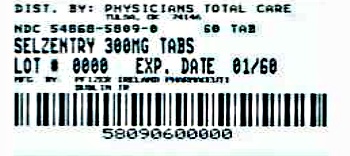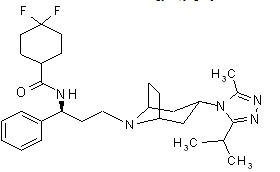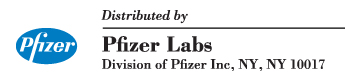 DRUG LABEL: SELZENTRY
NDC: 54868-5809 | Form: TABLET, FILM COATED
Manufacturer: Physicians Total Care, Inc.
Category: prescription | Type: HUMAN PRESCRIPTION DRUG LABEL
Date: 20120523

ACTIVE INGREDIENTS: Maraviroc 300 mg/1 1
INACTIVE INGREDIENTS: cellulose, microcrystalline; anhydrous dibasic calcium phosphate; sodium starch glycolate type A potato; magnesium stearate; FD&C blue no. 2; aluminum oxide; lecithin, soybean; polyethylene glycols; polyvinyl alcohol; talc; titanium dioxide

HIGHLIGHTS OF PRESCRIBING INFORMATION

These highlights do not include all the information needed to use SELZENTRY safely and effectively. See full prescribing information for SELZENTRY.
SELZENTRY (maraviroc) Tablets
Initial U.S. Approval: 2007

WARNING: HEPATOTOXICITY

See full prescribing information for complete boxed warning

- Hepatotoxicity has been reported which may be preceded by evidence of a systemic allergic reaction (e.g., pruritic rash, eosinophilia or elevated IgE).
- Immediately evaluate patients with signs or symptoms of hepatitis or allergic reaction. (5.1)

RECENT MAJOR CHANGES

Indication and Usage (1) | 11/2009
Dosage and Administration (2.2) | 05/2010
Contraindications (4) | 05/2010
Warnings and Precautions (5.2) | 05/2010
Warnings and Precautions (5.1), (5.2), (5.4), (5.5) | 11/2009

1 INDICATIONS AND USAGE

SELZENTRY is a CCR5 co-receptor antagonist indicated for combination antiretroviral treatment of adults infected with only CCR5-tropic HIV-1.

- In treatment-naïve subjects, more subjects treated with SELZENTRY experienced virologic failure and developed lamivudine resistance compared to efavirenz [see Microbiology (12.4) Clinical Studies (14.3)].
- Tropism testing with a highly sensitive tropism assay is required for the appropriate use of SELZENTRY (1).

2 DOSAGE AND ADMINISTRATION

When given with potent CYP3A inhibitors (with or without potent CYP3A inducers) including PIs (except tipranavir/ritonavir), delavirdine (2, 7.1) | 150 mg twice daily
With NRTIs, tipranavir/ritonavir, nevirapine, raltegravir, and other drugs that are not potent CYP3A inhibitors or CYP3A inducers (2, 7.1) | 300 mg twice daily
With potent CYP3A inducers including efavirenz (without a potent CYP3A inhibitor) (2, 7.1) | 600 mg twice daily

A more complete list of coadministered drugs is listed in Dosage and Administration (2).

Dose adjustment may be necessary in patients with renal impairment. (2.2).

3 DOSAGE FORMS AND STRENGTHS

Tablets: 150 mg and 300 mg (3)

4 CONTRAINDICATIONS

- SELZENTRY should not be used in patients with severe renal impairment or end-stage renal disease (ESRD) (CrCl < 30 mL/min) who are taking potent CYP3A inhibitors or inducers (4).

5 WARNINGS AND PRECAUTIONS

- Use caution when administering SELZENTRY to patients with pre-existing liver dysfunction or who are co-infected with viral hepatitis B or C (5.1).
- More cardiovascular events including myocardial ischemia and/or infarction were observed in treatment-experienced subjects who received SELZENTRY. Use with caution in patients at increased risk of cardiovascular events (5.2).
- If patients with severe renal impairment or end-stage renal disease (ESRD) receiving SELZENTRY (without concomitant CYP3A inducers or inhibitors) experience postural hypotension the SELZENTRY dose should be reduced from 300 mg twice daily to 150 mg twice daily (5.2).

6 Adverse Reactions

The most common adverse events in treatment-experienced subjects (>8% incidence) which occurred at a higher frequency compared to placebo are upper respiratory tract infections, cough, pyrexia, rash, and dizziness (6).

To report SUSPECTED ADVERSE REACTIONS, contact Pfizer at 1-800-438-1985 or FDA at 1-800-FDA-1088 or www.fda.gov/medwatch

7 DRUG INTERACTIONS

- Coadministration with CYP3A inhibitors, including protease inhibitors (except tipranavir/ritonavir) and delavirdine, will increase the concentration of SELZENTRY (7.1).
- Coadministration with CYP3A inducers, including efavirenz, may decrease the concentration of SELZENTRY (7.1).

8 USE IN SPECIFIC POPULATIONS

- SELZENTRY should only be used in pregnant women if the potential benefit justifies the potential risk to the fetus (8.1).
- There are no data available in pediatric patients; therefore, SELZENTRY should not be used in patients <16 years of age (8.4).

FULL PRESCRIBING INFORMATION

WARNING: HEPATOTOXICITY

Hepatotoxicity has been reported with SELZENTRY use. Evidence of a systemic allergic reaction (e.g., pruritic rash, eosinophilia or elevated IgE) prior to the development of hepatotoxicity may occur. Patients with signs or symptoms of hepatitis or allergic reaction following use of SELZENTRY should be evaluated immediately [see Warnings and Precautions (5.1)].

1 INDICATIONS AND USAGE

SELZENTRY, in combination with other antiretroviral agents, is indicated for adult patients infected with only CCR5-tropic HIV-1.

This indication is based on analyses of plasma HIV-1 RNA levels in two controlled studies of SELZENTRY in treatment-experienced subjects and one study in treatment-naïve subjects. Both studies in treatment-experienced subjects were conducted in clinically advanced, 3-class antiretroviral-experienced (NRTI, NNRTI, PI, or enfuvirtide) adults with evidence of HIV-1 replication despite ongoing antiretroviral therapy.

The following points should be considered when initiating therapy with SELZENTRY:

- Adult patients infected with only CCR5-tropic HIV-1 should use SELZENTRY.
- Tropism testing must be conducted with a highly sensitive tropism assay that has demonstrated the ability to identify patients appropriate for SELZENTRY use. Outgrowth of pre-existing low-level CXCR4- or dual/mixed-tropic HIV-1 not detected by tropism testing at screening has been associated with virologic failure on SELZENTRY. [see Microbiology (12.4) Clinical Studies (14.3)] .
- Use of SELZENTRY is not recommended in subjects with dual/mixed or CXCR4-tropic HIV-1 as efficacy was not demonstrated in a phase 2 study of this patient group.
- The safety and efficacy of SELZENTRY have not been established in pediatric patients.
- In treatment-naïve subjects, more subjects treated with SELZENTRY experienced virologic failure and developed lamivudine resistance compared to efavirenz. [see Microbiology (12.4) Clinical Studies (14.3)]

2 DOSAGE AND ADMINISTRATION

2.1 Dose Recommendations for Patients with Normal Renal Function

The recommended dose of SELZENTRY differs based on concomitant medications due to drug interactions (see Table 1). SELZENTRY can be taken with or without food. SELZENTRY must be given in combination with other antiretroviral medications.

Table 1 gives the recommended dose adjustments [see Drug Interactions (7.1)].

Table 1 Recommended Dosing Regimen
Concomitant Medications | SELZENTRY Dose
Potent CYP3A inhibitors (with or without a potent CYP3A inducer) including:; - protease inhibitors (except tipranavir/ritonavir) - delavirdine - ketoconazole, itraconazole, clarithromycin - other potent CYP3A inhibitors (e.g., nefazodone, telithromycin) | 150 mg twice daily
Other concomitant medications, including tipranavir/ritonavir, nevirapine, raltegravir all NRTIs and enfuvirtide | 300 mg twice daily
Potent CYP3A inducers (without a potent CYP3A inhibitor) including:; - efavirenz - rifampin - etravirine - carbamazepine, phenobarbital, and phenytoin | 600 mg twice daily

2.2 Dose Recommendations for Patients with Renal Impairment

Table 2 provides dosing recommendations for patients based on renal function and concomitant medications.

Table 2 Recommended Dosing Regimens Based on Renal Function
Concomitant Medications [See Table 1 for the list of concomitant medications.] | SELZENTRY Dose Based on Renal Function
Concomitant Medications [See Table 1 for the list of concomitant medications.] | Normal | Mild | Moderate | Severe | End Stage Renal Disease (ESRD)
Concomitant Medications [See Table 1 for the list of concomitant medications.] | CrCl >80 mL/min | CrCl >50 and ≤80 mL/min | CrCl ≥30 and ≤50 mL/min | CrCl <30 mL/min | On Regular Hemodialysis
Potent CYP3A inhibitors (with or without a CYP3A inducer) | 150 mg twice daily | 150 mg twice daily | 150 mg twice daily | NR | NR
Other concomitant medications* | 300 mg twice daily | 300 mg twice daily | 300 mg twice daily | 300 mg twice daily [The SELZENTRY dose should be reduced to 150 mg twice daily if there are any symptoms of postural hypotension [see Warnings and Precautions (5.2)].] | 300 mg twice daily
Potent CYP3A inducers (without a potent CYP3A inhibitor) | 600 mg twice daily | 600 mg twice daily | 600 mg twice daily | NR | NR
NR = not recommended

3 DOSAGE FORMS AND STRENGTHS

- 150 mg blue, oval film-coated tablets debossed with "Pfizer" on one side and "MVC 150" on the other
- 300 mg blue, oval film-coated tablets debossed with "Pfizer" on one side and "MVC 300" on the other

4 CONTRAINDICATIONS

SELZENTRY should not be used in patients with severe renal impairment or end-stage renal disease (ESRD) (CrCl < 30 mL/min) who are taking potent CYP3A inhibitors or inducers.

5 WARNINGS AND PRECAUTIONS

5.1 Hepatotoxicity

A case of possible SELZENTRY-induced hepatotoxicity with allergic features has been reported in a study of healthy volunteers. Discontinuation of SELZENTRY should be considered in any patient with signs or symptoms of hepatitis, or with increased liver transaminases combined with rash or other systemic symptoms.

The safety and efficacy of SELZENTRY have not been specifically studied in patients with significant underlying liver disorders. In studies of treatment-experienced HIV-infected subjects, approximately 6% of subjects were co-infected with hepatitis B and approximately 6% were co-infected with hepatitis C. Due to the small number of co-infected subjects studied, no conclusions can be drawn regarding whether they are at an increased risk for hepatic adverse events with SELZENTRY administration. However, caution should be used when administering SELZENTRY to patients with pre-existing liver dysfunction or who are co-infected with viral hepatitis B or C.

5.2 Cardiovascular Events

Use with caution in patients at increased risk for cardiovascular events. Eleven subjects (1.3%) who received SELZENTRY had cardiovascular events including myocardial ischemia and/or infarction during the Phase 3 studies in treatment-experienced studies [total exposure 609 patient-years (300 on once daily + 309 on twice daily SELZENTRY)], while no subjects who received placebo had such events (total exposure 111 patient-years). These subjects generally had cardiac disease or cardiac risk factors prior to SELZENTRY use, and the relative contribution of SELZENTRY to these events is not known.

In the Phase 2b/3 study in treatment-naïve subjects, 3 subjects (0.8%) who received SELZENTRY had events related to ischemic heart diseases and 5 subjects (1.4%) who received efavirenz had such events (total exposure 506 and 508 patient-years for SELZENTRY and efavirenz, respectively).

When SELZENTRY was administered to healthy volunteers at doses higher than the recommended dose, symptomatic postural hypotension was seen at a greater frequency than in placebo. However, when SELZENTRY was given at the recommended dose in HIV subjects in Phase 3 studies, postural hypotension was seen at a rate similar to placebo (approximately 0.5%). Caution should be used when administering SELZENTRY in patients with a history of postural hypotension or on concomitant medication known to lower blood pressure.

Postural Hypotension in Patients with Renal Impairment

Patients with impaired renal function may have cardiovascular co-morbidities and could be at increased risk of cardiovascular adverse events triggered by postural hypotension. An increased risk of postural hypotension may occur in patients with severe renal insufficiency or in those with end-stage renal disease (ESRD) due to increased maraviroc exposure in some patients. SELZENTRY should be used in patients with severe renal impairment or ESRD only if they are not receiving a concomitant potent CYP3A inhibitor or inducer. However, the use of SELZENTRY in these patients should only be considered when no alternative treatment options are available. If patients with severe renal impairment or ESRD experience any symptoms of postural hypotension while taking 300 mg twice daily the dose should be reduced to 150 mg twice daily [see Dosage and Administration (2.2)].

5.3 Immune Reconstitution Syndrome

Immune reconstitution syndrome has been reported in patients treated with combination antiretroviral therapy, including maraviroc. During the initial phase of combination antiretroviral treatment, patients whose immune system responds may develop an inflammatory response to indolent or residual opportunistic infections (such as infection with Mycobacterium avium, cytomegalovirus, Pneumocystis jirovecii, Mycobacterium tuberculosis, or reactivation of Herpes simplex and Herpes zoster), which may necessitate further evaluation and treatment.

5.4 Potential Risk of Infection

SELZENTRY antagonizes the CCR5 co-receptor located on some immune cells, and therefore could potentially increase the risk of developing infections. The overall incidence and severity of infection, as well as AIDS-defining category C infections, was comparable in the treatment groups during the Phase 3 treatment-experienced studies of SELZENTRY. While there was a higher rate of certain upper respiratory tract infections reported in the SELZENTRY arm compared to placebo (23% versus 13%), there was a lower rate of pneumonia (2% vs 5%) reported in subjects receiving SELZENTRY. A higher incidence of Herpes virus infections (11 per 100 patient-years) was also reported in the SELZENTRY arm when adjusted for exposure compared to placebo (8 per 100 patient-years).

In the Phase 2b/3 study in treatment-naïve subjects, the incidence of AIDS-defining Category C events when adjusted for exposure was 1.8 for SELZENTRY compared to 2.4 for efavirenz per 100 patient-years of exposure.

Patients should be monitored closely for evidence of infections while receiving SELZENTRY.

5.5 Potential Risk of Malignancy

While no increase in malignancy has been observed with SELZENTRY, due to this drug's mechanism of action it could affect immune surveillance and lead to an increased risk of malignancy.

The exposure-adjusted rate for malignancies per 100 patient-years of exposure in treatment-experienced studies was 4.6 for SELZENTRY compared to 9.3 on placebo. In treatment-naïve subjects, the rates were 1.0 and 2.4 per 100 patient-years of exposure for SELZENTRY and efavirenz, respectively.

Long-term follow-up is needed to more fully assess this risk.

6 Adverse Reactions

The following adverse reactions are discussed in other sections of the labeling:

- Hepatotoxicity [see Boxed Warning, Warnings and Precautions (5.1)]
- Cardiovascular events [see Warnings and Precautions (5.2)]

6.1 Clinical Trials Experience

Because clinical trials are conducted under widely varying conditions, adverse reaction rates observed in the clinical trials of a drug cannot be directly compared to rates in the clinical trials of another drug and may not reflect the rates observed in practice.

Studies in Treatment-Experienced Subjects

The safety profile of SELZENTRY is primarily based on 840 HIV-infected subjects who received at least one dose of SELZENTRY during two Phase 3 trials. A total of 426 of these subjects received the indicated twice daily dosing regimen.

Assessment of treatment-emergent adverse events is based on the pooled data from two studies in subjects with CCR5-tropic HIV-1 (A4001027 and A4001028). The median duration of maraviroc therapy for subjects in these studies was 48 weeks, with the total exposure on SELZENTRY twice daily at 309 patient-years versus 111 patient-years on placebo + OBT. The population was 89% male and 84% white, with mean age of 46 years (range 17–75 years). Subjects received dose equivalents of 300 mg maraviroc once or twice daily.

The most common adverse events reported with SELZENTRY twice daily therapy with frequency rates higher than placebo, regardless of causality, were upper respiratory tract infections, cough, pyrexia, rash, and dizziness. Additional adverse events that occurred with once daily dosing at a higher rate than both placebo and twice daily dosing were diarrhea, edema, influenza, esophageal candidiasis, sleep disorders, rhinitis, parasomnias, and urinary abnormalities. In these two studies, the rate of discontinuation due to adverse events was 5% for subjects who received SELZENTRY twice daily + optimized background therapy (OBT) as well as those who received placebo + OBT. Most of the adverse events reported were judged to be mild to moderate in severity. The data described below occurred with SELZENTRY twice daily dosing.

The total number of subjects reporting infections were 233 (55%) and 84 (40%) in the SELZENTRY twice daily and placebo groups, respectively. Correcting for the longer duration of exposure on SELZENTRY compared to placebo, the exposure-adjusted frequency (rate per 100 subject-years) of these events was 133 for both SELZENTRY twice daily and placebo.

Dizziness or postural dizziness occurred in 8% of subjects on either SELZENTRY or placebo, with 2 subjects (0.5%) on SELZENTRY permanently discontinuing therapy (1 due to syncope, 1 due to orthostatic hypotension) versus 1 subject on placebo (0.5%) permanently discontinuing therapy due to dizziness.

Treatment-emergent adverse events, regardless of causality, from A4001027 and A4001028 are summarized in Table 3. Selected events occurring at ≥2% of subjects and at a numerically higher rate in subjects treated with SELZENTRY are included; events that occurred at the same or higher rate on placebo are not displayed.

Table 3 Percentage of Subjects with Selected Treatment-Emergent Adverse Events (All Causality) (≥2% on SELZENTRY and at a higher rate compared to placebo) Studies A4001027 and A4001028 (Pooled Analysis, 48 Weeks)
 | SELZENTRY Twice Daily [300 mg dose equivalent] | Exposure-adjusted rate (per 100 pt-yrs) PYE=309 [PYE = patient years of exposure] | Placebo | Exposure-adjusted rate (per 100 pt-yrs) PYE=111
 | N=426 (%) |  | N=209 (%)
EYE DISORDERS
Conjunctivitis | 2 | 3 | 1 | 3
Ocular infections, inflammations and associated manifestations | 2 | 3 | 1 | 2
GASTROINTESTINAL DISORDERS
Constipation | 6 | 9 | 3 | 6
GENERAL DISORDERS AND ADMINISTRATION SITE CONDITIONS
Pyrexia | 13 | 20 | 9 | 17
Pain and discomfort | 4 | 5 | 3 | 5
INFECTIONS AND INFESTATIONS
Upper respiratory tract infection | 23 | 37 | 13 | 27
Herpes infection | 8 | 11 | 4 | 8
Sinusitis | 7 | 10 | 3 | 6
Bronchitis | 7 | 9 | 5 | 9
Folliculitis | 4 | 5 | 2 | 4
Pneumonia | 2 | 3 | 5 | 10
Anogenital warts | 2 | 3 | 1 | 3
Influenza | 2 | 3 | 0.5 | 1
Otitis media | 2 | 3 | 0.5 | 1
METABOLISM AND NUTRITION DISORDERS
Appetite disorders | 8 | 11 | 7 | 13
MUSCULOSKELETAL AND CONNECTIVE TISSUE DISORDERS
Joint related signs and symptoms | 7 | 10 | 3 | 5
Muscle pains | 3 | 4 | 0.5 | 1
NEOPLASMS BENIGN, MALIGNANT AND UNSPECIFIED
Skin neoplasms benign | 3 | 4 | 1 | 3
NERVOUS SYSTEM DISORDERS
Dizziness/postural dizziness | 9 | 13 | 8 | 17
Paresthesias and dysesthesias | 5 | 7 | 3 | 6
Sensory abnormalities | 4 | 6 | 1 | 3
Disturbances in consciousness | 4 | 5 | 3 | 6
Peripheral neuropathies | 4 | 5 | 3 | 6
PSYCHIATRIC DISORDERS
Disturbances in initiating and maintaining sleep | 8 | 11 | 5 | 10
Depressive disorders | 4 | 6 | 3 | 5
Anxiety symptoms | 4 | 5 | 3 | 7
RENAL AND URINARY DISORDERS
Bladder and urethral symptoms | 5 | 7 | 1 | 3
Urinary tract signs and symptoms | 3 | 4 | 1 | 3
RESPIRATORY, THORACIC AND MEDIASTINAL DISORDERS
Coughing and associated symptoms | 14 | 21 | 5 | 10
Upper respiratory tract signs and symptoms | 6 | 9 | 3 | 6
Nasal congestion and inflammations | 4 | 6 | 3 | 5
Breathing abnormalities | 4 | 5 | 2 | 5
Paranasal sinus disorders | 3 | 4 | 0.5 | 1
SKIN AND SUBCUTANEOUS TISSUE DISORDERS
Rash | 11 | 16 | 5 | 11
Apocrine and eccrine gland disorders | 5 | 7 | 4 | 7.5
Pruritus | 4 | 5 | 2 | 4
Lipodystrophies | 3 | 5 | 0.5 | 1
Erythemas | 2 | 3 | 1 | 2
VASCULAR DISORDERS
Vascular hypertensive disorders | 3 | 4 | 2 | 4

Laboratory Abnormalities

Table 4 shows the treatment-emergent Grade 3–4 laboratory abnormalities that occurred in >2% of subjects receiving SELZENTRY.

Table 4 Maximum Shift in Laboratory Test Values (Without Regard to Baseline) Incidence ≥2% of Grade 3–4 Abnormalities (ACTG Criteria) Studies A4001027 and A4001028 (Pooled Analysis, 48 Weeks)
Laboratory Parameter Preferred Term | Limit | SELZENTRY Twice daily + OBT | Placebo + OBT
 |  | N =421 [Percentages based on total subjects evaluated for each laboratory parameter] % | N =207 %
Aspartate aminotransferase | >5.0× ULN | 4.8 | 2.9
Alanine aminotransferase | >5.0× ULN | 2.6 | 3.4
Total bilirubin | >5.0× ULN | 5.5 | 5.3
Amylase | >2.0× ULN | 5.7 | 5.8
Lipase | >2.0× ULN | 4.9 | 6.3
Absolute neutrophil count | <750/mm^3 | 4.3 | 2.4

Study in Treatment-Naïve Subjects

Treatment-Emergent Adverse Events

Treatment-emergent adverse events, regardless of causality, from Study A4001026, a double-blind comparative controlled study in which 721 treatment-naïve subjects received SELZENTRY 300 mg BID (N=360) or efavirenz (N=361) in combination with zidovudine/lamivudine for 96 weeks, are summarized in Table 5. Selected events occurring at ≥ 2% of subjects and at a numerically higher rate in subjects treated with SELZENTRY are included; events that occurred at the same or higher rate on efavirenz are not displayed.

Table 5 Percentage of Subjects with Selected Treatment-Emergent Adverse Events (All Causality) (≥2% on SELZENTRY and at a higher rate compared to efavirenz) Study A4001026 (96 Weeks)
 | SELZENTRY + zidovudine/lamivudine 300 mg BID N = 360 (%) | EFAVIRENZ + zidovudine/lamivudine 600 mg QD N = 361 (%)
BLOOD AND LYMPHATIC SYSTEM DISORDERS
Anemias NEC | 8 | 5
Neutropenias | 4 | 3
EAR AND LABYRINTH DISORDERS
Ear disorders NEC | 3 | 2
GASTROINTESTINAL DISORDERS
Flatulence, bloating and distention | 10 | 7
Gastrointestinal atonic and hypomotility disorders NEC | 9 | 5
Gastrointestinal signs and symptoms NEC | 3 | 2
GENERAL DISORDERS AND ADMINISTRATION SITE CONDITIONS
Body Temperature perception | 3 | 1
INFECTIONS AND INFESTATIONS
Bronchitis | 13 | 9
Herpes Infection | 7 | 6
Upper Respiratory Tract Infection | 32 | 30
Bacterial infections NEC | 6 | 3
Herpes zoster/varicella | 5 | 4
Lower respiratory tract and lung infections | 3 | 2
Neisseria infections | 3 | 0
Tinea infections | 4 | 3
Viral infections NEC | 3 | 2
MUSCULOSKELETAL AND CONNECTIVE TISSUE DISORDERS
Joint related signs and symptoms | 6 | 5
NERVOUS SYSTEM DISORDERS
Memory loss (excluding dementia) | 3 | 1
Parasthesias and Dyesthesias | 4 | 3
RENAL AND URINARY DISORDERS
Bladder and urethral symptoms | 4 | 3
REPRODUCTIVE SYSTEM AND BREAST DISORDERS
Erection and ejaculation conditions and disorders | 3 | 2
RESPIRATORY, THORACIC AND MEDIASTINAL DISORDERS
Upper respiratory tract signs and symptoms | 9 | 5
SKIN AND SUBCUTANEOUS TISSUE DISORDERS
Acnes | 3 | 2
Alopecias | 2 | 1
Lipodystrophies | 4 | 3
Nail and nail bed conditions (excluding infections and infestations) | 6 | 2

Laboratory Abnormalities

Table 6 Maximum Shift in Laboratory Test Values (Without Regard to Baseline) Incidence ≥2% of Grade 3–4 Abnormalities (ACTG Criteria) Study A4001026 (96 Weeks)
Laboratory Parameter Preferred Term | Limit | SELZENTRY 300 Twice daily + zidovudine/lamivudine N =353 [N = total number of subjects evaluable for laboratory abnormalities.] % | Efavirenz 600 mg QD + zidovudine/lamivudine N =350 %
Aspartate aminotransferase | >5.0× ULN | 4.0 | 4.0
Alanine aminotransferase | >5.0× ULN | 3.9 | 4.0
Creatine kinase |  | 3.9 | 4.8
Amylase | >2.0× ULN | 4.3 | 6.0
Absolute neutrophil count | <750/mm^3 | 5.7 | 4.9
Hemoglobin | <7.0 g/dL | 2.9 | 2.3
Percentages based on total subjects evaluated for each laboratory parameter. If the same subject in a given treatment group had >1 occurrence of the same abnormality, only the most severe is counted.

Less Common Adverse Events in Clinical Trials

The following adverse events occurred in <2% of SELZENTRY-treated subjects. These events have been included because of their seriousness and either increased frequency on SELZENTRY or are potential risks due to the mechanism of action. Events attributed to the patient's underlying HIV infection are not listed.

Blood and Lymphatic System: marrow depression and hypoplastic anemia

Cardiac Disorders: unstable angina, acute cardiac failure, coronary artery disease, coronary artery occlusion, myocardial infarction, myocardial ischemia

Hepatobiliary Disorders: hepatic cirrhosis, hepatic failure, cholestatic jaundice, portal vein thrombosis, hypertransaminasemia, jaundice

Infections and Infestations: endocarditis, infective myositis, viral meningitis, pneumonia, treponema infections, septic shock, Clostridium difficile colitis, meningitis

Musculoskeletal and Connective Tissue Disorders: myositis, osteonecrosis, rhabdomyolysis, blood CK increased

Neoplasms benign, Malignant and Unspecified (including Cysts and Polyps): abdominal neoplasm, anal cancer, basal cell carcinoma, Bowen's disease, cholangiocarcinoma, diffuse large B-cell lymphoma, lymphoma, metastases to liver, esophageal carcinoma, nasopharyngeal carcinoma, squamous cell carcinoma, squamous cell carcinoma of skin, tongue neoplasm (malignant stage unspecified), anaplastic large cell lymphomas T- and null-cell types, bile duct neoplasms malignant, endocrine neoplasms malignant and unspecified

Nervous System Disorders: cerebrovascular accident, convulsions and epilepsy, tremor (excluding congenital), facial palsy, hemianopia, loss of consciousness, visual field defect

6.2 Postmarketing Experience

The following events have been identified during post-approval use of SELZENTRY. Because these reactions are reported voluntarily from a population of unknown size, it is not possible to estimate their frequency or establish a causal relationship to SELZENTRY exposure.

Skin and Subcutaneous Tissue Disorders
Stevens-Johnson syndrome.

7 DRUG INTERACTIONS

7.1 Effect of Concomitant Drugs on the Pharmacokinetics of Maraviroc

Maraviroc is a substrate of CYP3A and Pgp and hence its pharmacokinetics are likely to be modulated by inhibitors and inducers of these enzymes/transporters. Therefore, a dose adjustment may be required when maraviroc is coadministered with those drugs [see Dosage and Administration (2)].

Concomitant use of maraviroc and St. John's wort (hypericum perforatum) or products containing St. John's wort is not recommended. Coadministration of maraviroc with St. John's wort is expected to substantially decrease maraviroc concentrations and may result in suboptimal levels of maraviroc and lead to loss of virologic response and possible resistance to maraviroc.

For additional drug interaction information see Clinical Pharmacology (12.3).

8 USE IN SPECIFIC POPULATIONS

8.1 Pregnancy

TERATOGENIC EFFECTS

Pregnancy Category B

The incidence of fetal variations and malformations was not increased in embryofetal toxicity studies performed with maraviroc in rats at exposures (AUC) approximately 20-fold higher and in rabbits at approximately 5-fold higher than human exposures at the recommended daily dose (up to 1000 mg/kg/day in rats and 75 mg/kg/day in rabbits). During the pre- and postnatal development studies in the offspring, development of the offspring, including fertility and reproductive performance, was not affected by the maternal administration of maraviroc.

However, there are no adequate and well-controlled studies in pregnant women. Because animal reproduction studies are not always predictive of human response, SELZENTRY should be used during pregnancy only if clearly needed.

Antiretroviral Pregnancy Registry

To monitor maternal-fetal outcomes of pregnant women exposed to SELZENTRY and other antiretroviral agents, an Antiretroviral Pregnancy Registry has been established. Physicians are encouraged to register patients by calling 1-800-258-4263.

8.3 Nursing Mothers

The Centers for Disease Control and Prevention recommend that HIV-infected mothers not breastfeed their infants to avoid risking postnatal transmission of HIV infection. Studies in lactating rats indicate that maraviroc is extensively secreted into rat milk. It is not known whether maraviroc is secreted into human milk. Because of the potential for both HIV transmission and serious adverse reactions in nursing infants, mothers should be instructed not to breastfeed if they are receiving SELZENTRY.

8.4 Pediatric Use

The pharmacokinetics, safety and efficacy of maraviroc in patients <16 years of age have not been established. Therefore, maraviroc should not be used in this patient population.

8.5 Geriatric Use

There were insufficient numbers of subjects aged 65 and over in the clinical studies to determine whether they respond differently from younger subjects. In general, caution should be exercised when administering SELZENTRY in elderly patients, also reflecting the greater frequency of decreased hepatic and renal function, of concomitant disease and other drug therapy.

8.6 Renal Impairment

Recommended doses of SELZENTRY for patients with impaired renal function (CrCl ≤ 80 mL/min) are based on the results of a pharmacokinetic study conducted in healthy subjects with various degrees of renal impairment. The pharmacokinetics of maraviroc in subjects with mild and moderate renal impairment was similar to that in subjects with normal renal function [see Clinical Pharmacology (12.3)]. A limited number of subjects with mild and moderate renal impairment in the Phase 3 clinical trials (n= 131 and n= 12, respectively) received the same dose of SELZENTRY as that administered to subjects with normal renal function. In these subjects there was no apparent difference in the adverse event profile for maraviroc compared to subjects with normal renal function.

If patients with severe renal impairment or end-stage renal disease (ESRD) not receiving a concomitant potent CYP3A inhibitor or inducer experience any symptoms of postural hypotension while taking SELZENTRY 300 mg twice daily, the dose should be reduced to 150 mg twice daily. No studies have been performed in subjects with severe renal impairment or ESRD co-treated with potent CYP3A inhibitors or inducers. Hence, no dose of SELZENTRY can be recommended, and SELZENTRY is contraindicated for these patients. [see Dosage and Administration (2.2), Contraindications (4), Warnings and Precautions (5.2), and Clinical Pharmacology (12.3)].

8.7 Hepatic Impairment

Maraviroc is principally metabolized by the liver; therefore, caution should be exercised when administering this drug to patients with hepatic impairment, because maraviroc concentrations may be increased. Maraviroc concentrations are higher when SELZENTRY 150 mg is administered with a potent CYP3A inhibitor compared to following administration of 300 mg without a CYP3A inhibitor, so patients with moderate hepatic impairment who receive SELZENTRY 150 mg with a potent CYP3A inhibitor should be monitored closely for maraviroc-associated adverse events. Maraviroc has not been studied in subjects with severe hepatic impairment [see Warnings and Precautions (5.1) and Clinical Pharmacology (12.3)].

8.8 Gender

Population pharmacokinetic analysis of pooled Phase 1/2a data indicated gender (female: n=96, 23.2% of the total population) does not affect maraviroc concentrations. Dosage adjustment based on gender is not necessary.

8.9 Race

Population pharmacokinetic analysis of pooled Phase 1/2a data indicated exposure was 26.5% higher in Asians (N=95) as compared to non-Asians (n=318). However, a study designed to evaluate pharmacokinetic differences between Caucasians (n=12) and Singaporeans (n=12) showed no difference between these two populations. No dose adjustment based on race is needed.

10 OVERDOSAGE

The highest dose administered in clinical studies was 1200 mg. The dose-limiting adverse event was postural hypotension, which was observed at 600 mg. While the recommended dose for SELZENTRY in patients receiving a CYP3A inducer without a CYP3A inhibitor is 600 mg twice daily, this dose is appropriate due to enhanced metabolism.

Prolongation of the QT interval was seen in dogs and monkeys at plasma concentrations 6 and 12 times, respectively, those expected in humans at the intended exposure of 300 mg equivalents twice daily. However, no significant QT prolongation was seen in the studies in treatment-experienced subjects with HIV using the recommended doses of maraviroc or in a specific pharmacokinetic study to evaluate the potential of maraviroc to prolong the QT interval [see Clinical Pharmacology (12.3)].

There is no specific antidote for overdose with maraviroc. Treatment of overdose should consist of general supportive measures including keeping the patient in a supine position, careful assessment of patient vital signs, blood pressure and ECG.

If indicated, elimination of unabsorbed active maraviroc should be achieved by emesis or gastric lavage. Administration of activated charcoal may also be used to aid in removal of unabsorbed drug. Since maraviroc is moderately protein-bound, dialysis may be beneficial in removal of this medicine.

11 DESCRIPTION

SELZENTRY (maraviroc) is a selective, slowly reversible, small molecule antagonist of the interaction between human CCR5 and HIV-1 gp120. Blocking this interaction prevents CCR5-tropic HIV-1 entry into cells.

SELZENTRY is available as film-coated tablets for oral administration containing either 150 or 300 mg of maraviroc and the following inactive ingredients: microcrystalline cellulose, dibasic calcium phosphate (anhydrous), sodium starch glycolate, and magnesium stearate. The film coat [Opadry® II Blue (85G20583)] contains FD&C blue #2 aluminum lake, soya lecithin, polyethylene glycol (macrogol 3350), polyvinyl alcohol, talc and titanium dioxide.

Maraviroc is chemically described as 4,4-difluoro-N-{(1S)-3-[exo-3-(3-isopropyl-5-methyl-4H-1,2,4-triazol-4-yl)-8-azabicyclo[3.2.1]oct-8-yl]-1-phenylpropyl}cyclohexanecarboxamide.

The molecular formula is C29H41F2N5O and the structural formula is:

Maraviroc is a white to pale colored powder with a molecular weight of 513.67. It is highly soluble across the physiological pH range (pH 1.0 to 7.5).

12 CLINICAL PHARMACOLOGY

12.1 Mechanism of Action

Maraviroc is an antiviral drug [see Clinical Pharmacology (12.4)].

12.2 Pharmacodynamics

Exposure Response Relationship in Treatment-Experienced Subjects

The relationship between maraviroc, modeled plasma trough concentration (Cmin) (1–9 samples per patient taken on up to 7 visits), and virologic response was evaluated in 973 treatment-experienced HIV-1-infected subjects with varied optimized background antiretroviral regimens in studies A4001027 and A4001028. The Cmin, baseline viral load, baseline CD4^+ cell count and overall sensitivity score (OSS) were found to be important predictors of virologic success (defined as viral load < 400 copies/mL at 24 weeks). Table 7 illustrates the proportion of subjects with virologic success (%) within each Cmin quartile for 150 mg twice daily and 300 mg twice daily groups.

Table 7 Treatment-Experienced Subjects with Virologic Success by Cmin Quartile (Q1–Q4))
 | 150 mg BID (with CYP3A inhibitors) |  |  | 300 mg BID (without CYP3A inhibitors)
 | n | Median Cmin | % subjects with virologic success | n | Median Cmin | % subjects with virologic success
Placebo | 160 | - | 30.6 | 35 | - | 28.6
Q1 | 78 | 33 | 52.6 | 22 | 13 | 50.0
Q2 | 77 | 87 | 63.6 | 22 | 29 | 68.2
Q3 | 78 | 166 | 78.2 | 22 | 46 | 63.6
Q4 | 78 | 279 | 74.4 | 22 | 97 | 68.2

Exposure Response Relationship in Treatment-Naive Subjects

The relationship between maraviroc, modeled plasma trough concentration (Cmin) (1–12 samples per patient taken on up to 8 visits), and virologic response was evaluated in 294 treatment-naive HIV-1-infected subjects receiving maraviroc 300 mg twice daily in combination with zidovudine/lamivudine in study A4001026. Table 8 illustrates the proportion (%) of subjects with virologic success < 50 copies/mL at 48 weeks within each Cmin quartile for the 300 mg twice daily dose.

Table 8 Treatment-Naïve Subjects with Virologic Success by Cmin Quartile (Q1–Q4)
 | 300 mg BID
 | n | Median Cmin | % subjects with virologic success
Q1 | 75 | 23 | 57.3
Q2 | 72 | 39 | 72.2
Q3 | 73 | 56 | 74.0
Q4 | 74 | 81 | 83.8
Eighteen of 75 (24%) subjects in Q1 had no measurable maraviroc concentration on at least one occasion vs. 1 of 73 and 1 of 74 in quartiles 3 and 4 respectively.

Effects on Electrocardiogram

A placebo-controlled, randomized, crossover study to evaluate the effect on the QT interval of healthy male and female volunteers was conducted with three single oral doses of maraviroc and moxifloxacin. The placebo-adjusted mean maximum (upper 1-sided 95% CI) increases in QTc from baseline after 100, 300 and 900 mg of maraviroc were –2 (0), -1 (1), and 1 (3) msec, respectively, and 13 (15) msec for moxifloxacin 400 mg. No subject in any group had an increase in QTc of ≥60 msec from baseline. No subject experienced an interval exceeding the potentially clinically relevant threshold of 500 msec.

12.3 Pharmacokinetics

Table 9 Mean Maraviroc Pharmacokinetic Parameters
 | Maraviroc dose | N | AUC12 (ng.h/Ml) | Cmax (ng/mL) | Cmin (ng/mL)
Healthy volunteers (phase 1) | 300 mg twice daily | 64 | 2908 | 888 | 43.1
Asymptomatic HIV subjects (phase 2a) | 300 mg twice daily | 8 | 2550 | 618 | 33.6
Treatment-experienced HIV subjects (phase 3) [The estimated exposure is lower compared to other studies possibly due to sparse sampling, food effect, compliance and concomitant medications.] | 300 mg twice daily | 94 | 1513 | 266 | 37.2
Treatment-experienced HIV subjects (phase 3) [The estimated exposure is lower compared to other studies possibly due to sparse sampling, food effect, compliance and concomitant medications.] | 150 mg twice daily (+ CYP3A inhibitor) | 375 | 2463 | 332 | 101
Treatment-naïve HIV subjects (phase 2b/3) | 300 mg twice daily | 344 | 1865 | 287 | 60

Absorption

Peak maraviroc plasma concentrations are attained 0.5–4h following single oral doses of 1–1200 mg administered to uninfected volunteers. The pharmacokinetics of oral maraviroc are not dose-proportional over the dose range.

The absolute bioavailability of a 100 mg dose is 23% and is predicted to be 33% at 300 mg. Maraviroc is a substrate for the efflux transporter P-glycoprotein.

Effect of Food on Oral Absorption

Coadministration of a 300mg tablet with a high fat breakfast reduced maraviroc Cmax and AUC by 33% in healthy volunteers. There were no food restrictions in the studies that demonstrated the efficacy and safety of maraviroc [see Clinical Studies (14)]. Therefore, maraviroc can be taken with or without food at the recommended dose [see Dosage and Administration (2)].

Distribution

Maraviroc is bound (approximately 76%) to human plasma proteins, and shows moderate affinity for albumin and alpha-1 acid glycoprotein. The volume of distribution of maraviroc is approximately 194L.

Metabolism

Studies in humans and in vitro studies using human liver microsomes and expressed enzymes have demonstrated that maraviroc is principally metabolized by the cytochrome P450 system to metabolites that are essentially inactive against HIV-1. In vitro studies indicate that CYP3A is the major enzyme responsible for maraviroc metabolism. In vitro studies also indicate that polymorphic enzymes CYP2C9, CYP2D6 and CYP2C19 do not contribute significantly to the metabolism of maraviroc.

Maraviroc is the major circulating component (~42% drug-related radioactivity) following a single oral dose of 300 mg[^14C]-maraviroc. The most significant circulating metabolite in humans is a secondary amine (~22% radioactivity) formed by N-dealkylation. This polar metabolite has no significant pharmacological activity. Other metabolites are products of mono-oxidation and are only minor components of plasma drug-related radioactivity.

Excretion

The terminal half-life of maraviroc following oral dosing to steady state in healthy subjects was 14–18 hours. A mass balance/excretion study was conducted using a single 300mg dose of ^14C-labeled maraviroc. Approximately 20% of the radiolabel was recovered in the urine and 76% was recovered in the feces over 168 hours. Maraviroc was the major component present in urine (mean of 8% dose) and feces (mean of 25% dose). The remainder was excreted as metabolites.

Hepatic Impairment

Maraviroc is primarily metabolized and eliminated by the liver. A study compared the pharmacokinetics of a single 300 mg dose of SELZENTRY in subjects with mild (Child-Pugh Class A, n=8), and moderate (Child-Pugh Class B, n=8) hepatic impairment to pharmacokinetics in healthy subjects (n=8). The mean Cmax and AUC were 11% and 25% higher, respectively, for subjects with mild hepatic impairment, and 32% and 46% higher, respectively, for subjects with moderate hepatic impairment compared to subjects with normal hepatic function. These changes do not warrant a dose adjustment. Maraviroc concentrations are higher when SELZENTRY 150 mg is administered with a potent CYP3A inhibitor compared to following administration of 300 mg without a CYP3A inhibitor, so patients with moderate hepatic impairment who receive SELZENTRY 150 mg with a potent CYP3A inhibitor should be monitored closely for maraviroc-associated adverse events. The pharmacokinetics of maraviroc have not been studied in subjects with severe hepatic impairment [see Warnings and Precautions (5.1)].

Renal Impairment

A study compared the pharmacokinetics of a single 300 mg dose of SELZENTRY in subjects with severe renal impairment (CLcr < 30 mL/min, n=6) and end-stage renal disease (ESRD) (n=6) to healthy volunteers (n=6). Geometric mean ratios for maraviroc Cmax and AUCinf were 2.4-fold and 3.2-fold higher respectively for subjects with severe renal impairment, and 1.7-fold and 2.0-fold higher respectively for subjects with ESRD as compared to subjects with normal renal function in this study. Hemodialysis had a minimal effect on maraviroc clearance and exposure in subjects with ESRD. Exposures observed in subjects with severe renal impairment and ESRD were within the range observed in previous SELZENTRY 300 mg single-dose studies in healthy volunteers with normal renal function. However, maraviroc exposures in the subjects with normal renal function in this study were 50% lower than that observed in previous studies. Based on the results of this study, no dose adjustment is recommended for patients with renal impairment receiving SELZENTRY without a potent CYP3A inhibitor or inducer. However, if patients with severe renal impairment or ESRD experience any symptoms of postural hypotension while taking SELZENTRY 300 mg twice daily, their dose should be reduced to 150 mg twice daily [see Dosage and Administration (2.2); Warnings and Precautions (5.2)].

In addition, the study compared the pharmacokinetics of multiple dose SELZENTRY in combination with saquinavir/ritonavir 1000/100 mg twice daily (a potent CYP3A inhibitor combination) for 7 days in subjects with mild renal impairment (CLcr >50 and ≤80 mL/min, n=6) and moderate renal impairment (CLcr ≥30 and ≤50 mL/min, n=6) to healthy volunteers with normal renal function (n=6). Subjects received 150 mg of SELZENTRY at different dose frequencies (healthy volunteers – every 12 hours; mild renal impairment – every 24 hours; moderate renal impairment – every 48 hours). Compared to healthy volunteers (dosed every 12 hours), geometric mean ratios for maraviroc AUCtau, Cmax and Cmin were 50% higher, 20% higher and 43% lower, respectively for subjects with mild renal impairment (dosed every 24 hours). Geometric mean ratios for maraviroc AUCtau, Cmax and Cmin were 16% higher, 29% lower and 85% lower, respectively for subjects with moderate renal impairment (dosed every 48 hours) compared to healthy volunteers (dosed every 12 hours). Based on the data from this study, no adjustment in dose is recommended for patients with mild or moderate renal impairment [see Dosage and Administration (2.2)].

Effect of Concomitant Drugs on the Pharmacokinetics of Maraviroc

Maraviroc is a substrate of CYP3A and Pgp and hence its pharmacokinetics are likely to be modulated by inhibitors and inducers of these enzymes/transporters. The CYP3A/Pgp inhibitors ketoconazole, lopinavir/ritonavir, ritonavir, darunavir/ritonavir, saquinavir/ritonavir and atazanavir ± ritonavir all increased the Cmax and AUC of maraviroc [see Table 10]. The CYP3A inducers rifampin, etravirine and efavirenz decreased the Cmax and AUC of maraviroc [see Table 10].

Tipranavir/ritonavir (net CYP3A inhibitor/Pgp inducer) did not affect the steady state pharmacokinetics of maraviroc (see Table 10). Co-trimoxazole and tenofovir did not affect the pharmacokinetics of maraviroc.

Table 10 Effect of Coadministered Agents on the Pharmacokinetics of Maraviroc
Coadministered drug and dose | N | Maraviroc Dose | Ratio (90% CI) of maraviroc pharmacokinetic parameters with/without coadministered drug (no effect = 1.00)
Coadministered drug and dose | N | Maraviroc Dose | Cmin | AUCtau | Cmax
CYP3A and/or P-gp Inhibitors
Ketoconazole 400 mg QD | 12 | 100 mg BID | 3.75 (3.01, 4.69) | 5.00 (3.98, 6.29) | 3.38 (2.38, 4.78)
Ritonavir 100 mg BID | 8 | 100 mg BID | 4.55 (3.37, 6.13) | 2.61 (1.92, 3.56) | 1.28 (0.79, 2.09)
Saquinavir (soft gel capsules) /ritonavir 1000 mg/100 mg BID | 11 | 100 mg BID | 11.3 (8.96, 14.1) | 9.77 (7.87, 12.14) | 4.78 (3.41, 6.71)
Lopinavir/ritonavir 400 mg/100 mg BID | 11 | 300 mg BID | 9.24 (7.98, 10.7) | 3.95 (3.43, 4.56) | 1.97 (1.66, 2.34)
Atazanavir 400 mg QD | 12 | 300 mg BID | 4.19 (3.65, 4.80) | 3.57 (3.30, 3.87) | 2.09 (1.72, 2.55)
Atazanavir/ritonavir 300 mg/100 mg QD | 12 | 300 mg BID | 6.67 (5.78, 7.70) | 4.88 (4.40, 5.41) | 2.67 (2.32, 3.08)
Darunavir/ritonavir 600 mg/100 mg BID | 12 | 150 mg BID | 8.00 (6.35, 10.1) | 4.05 2.94, 5.59 | 2.29 (1.46, 3.59)
CYP3A and/or P-gp Inducers
Efavirenz 600 mg QD | 12 | 100 mg BID | 0.55 (0.43, 0.72) | 0.552 (0.492, 0.620) | 0.486 (0.377, 0.626)
Efavirenz 600 mg QD | 12 | 200 mg BID (+efavirenz): 100 mg BID (alone) | 1.09 (0.89, 1.35) | 1.15 (0.98, 1.35) | 1.16 (0.87, 1.55)
Rifampicin 600 mg QD | 12 | 100 mg BID | 0.22 (0.17, 0.28) | 0.368 (0.328, 0.413) | 0.335 (0.260, 0.431)
Rifampicin 600 mg QD | 12 | 200 mg BID (+rifampicin): 100 mg BID (alone) | 0.66 (0.54, 0.82) | 1.04 (0.89, 1.22) | 0.97 (0.72, 1.29)
Etravirine 200 mg BID | 14 | 300 mg BID | 0.609 (0.525, 0.707) | 0.468 (0.381, 0.576) | 0.400 (0.282, 0.566)
Nevirapine [Compared to historical data] 200 mg BID (+ lamivudine 150 mg BID, tenofovir 300 mg QD) | 8 | 300 mg SD | - | 1.01 (0.65, 1.55) | 1.54 (0.94, 2.51)
CYP3A and/or P-gp Inhibitors and Inducers
Lopinavir/ritonavir + efavirenz 400 mg/100 mg BID + 600 mg QD | 11 | 300 mg BID | 6.29 (4.72, 8.39) | 2.53 (2.24, 2.87) | 1.25 (1.01, 1.55)
Saquinavir(soft gel capsules) /ritonavir + efavirenz 1000 mg/100 mg BID + 600 mg QD | 11 | 100 mg BID | 8.42 (6.46, 10.97) | 5.00 (4.26, 5.87) | 2.26 (1.64, 3.11)
Darunavir/ritonavir + etravirine 600 mg/100 mg BID + 200 mg BID | 10 | 150 mg BID | 5.27 (4.51, 6.15) | 3.10 (2.57, 3.74) | 1.77 (1.20, 2.60)
Tipranavir/ritonavir 500 mg/200 mg BID | 12 | 150 mg BID | 1.80 (1.55, 2.09) | 1.02 (0.850, 1.23) | 0.86 (0.61, 1.21)
Other
Raltegravir 400 mg BID | 17 | 300 mg BID | 0.90 (0.85, 0.96) | 0.86 (0.80, 0.92) | 0.79 (0.67, 0.94)

Effect of Maraviroc on the Pharmacokinetics of Concomitant Drugs

Maraviroc is unlikely to inhibit the metabolism of coadministered drugs metabolized by the following cytochrome P enzymes (CYP1A2, CYP2B6, CYP2C8, CYP2C9, CYP2C19, and CYP3A) because maraviroc did not inhibit activity of those enzymes at clinically relevant concentrations in vitro. Maraviroc does not induce CYP1A2 in vitro.

In vitro results indicate that maraviroc could inhibit P-glycoprotein in the gut and may thus affect bioavailability of certain drugs.

Drug interaction studies were performed with maraviroc and other drugs likely to be coadministered or commonly used as probes for pharmacokinetic interactions [see Table 6]. Maraviroc had no effect on the pharmacokinetics of zidovudine or lamivudine. Maraviroc decreased the Cmin and AUC of raltegravir by 27% and 37%, respectively, which is not clinically significant. Maraviroc had no clinically relevant effect on the pharmacokinetics of midazolam, the oral contraceptives ethinylestradiol and levonorgestrel, no effect on the urinary 6β-hydroxycortisol/cortisol ratio, suggesting no induction of CYP3A in vivo. Maraviroc had no effect on the debrisoquine metabolic ratio (MR) at 300 mg twice daily or less in vivo and did not cause inhibition of CYP2D6 in vitro until concentrations >100µM. However, there was 234% increase in debrisoquine MR on treatment compared to baseline at 600 mg once daily, suggesting potential inhibition of CYP2D6 at higher dose.

12.4 Microbiology

Mechanism of Action

Maraviroc is a member of a therapeutic class called CCR5 co-receptor antagonists. Maraviroc selectively binds to the human chemokine receptor CCR5 present on the cell membrane, preventing the interaction of HIV-1 gp120 and CCR5 necessary for CCR5-tropic HIV-1 to enter cells. CXCR4-tropic and dual-tropic HIV-1 entry is not inhibited by maraviroc.

Antiviral Activity in Cell Culture

Maraviroc inhibits the replication of CCR5-tropic laboratory strains and primary isolates of HIV-1 in models of acute peripheral blood leukocyte infection. The mean EC50 value (50% effective concentration) for maraviroc against HIV-1 group M isolates (subtypes A to J and circulating recombinant form AE) and group O isolates ranged from 0.1 to 4.5 nM (0.05 to 2.3 ng/mL) in cell culture.

When used with other antiretroviral agents in cell culture, the combination of maraviroc was not antagonistic with NNRTIs (delavirdine, efavirenz and nevirapine), NRTIs (abacavir, didanosine, emtricitabine, lamivudine, stavudine, tenofovir, zalcitabine and zidovudine), or protease inhibitors (amprenavir, atazanavir, darunavir, indinavir, lopinavir, nelfinavir, ritonavir, saquinavir and tipranavir). Maraviroc was additive/synergistic with the HIV fusion inhibitor enfuvirtide. Maraviroc was not active against CXCR4-tropic and dual-tropic viruses (EC50 value >10 µM). The antiviral activity of maraviroc against HIV-2 has not been evaluated.

Resistance in Cell Culture

HIV-1 variants with reduced susceptibility to maraviroc have been selected in cell culture, following serial passage of two CCR5-tropic viruses (CC1/85 and RU570). The maraviroc-resistant viruses remained CCR5-tropic with no evidence of a change from a CCR5-tropic virus to a CXCR4-using virus. Two amino acid residue substitutions in the V3-loop region of the HIV-1 envelope glycoprotein (gp160), A316T and I323V (HXB2 numbering), were shown to be necessary for the maraviroc-resistant phenotype in the HIV-1 isolate CC1/85. In the RU570 isolate a 3-amino acid residue deletion in the V3 loop, ΔQAI (HXB2 positions 315–317), was associated with maraviroc resistance. The relevance of the specific gp120 mutations observed in maraviroc-resistant isolates selected in cell culture to clinical maraviroc resistance is not known. Maraviroc-resistant viruses were characterized phenotypically by concentration response curves that did not reach 100% inhibition in phenotypic drug assays, rather than increases in EC50 values.

Cross-resistance in Cell Culture

Maraviroc had antiviral activity against HIV-1 clinical isolates resistant to NNRTIs, NRTIs, PIs and the fusion inhibitor enfuvirtide in cell culture (EC50 values ranged from 0.7 to 8.9 nM (0.36 to 4.57 ng/mL)). Maraviroc-resistant viruses that emerged in cell culture remained susceptible to the enfuvirtide and the protease inhibitor saquinavir.

Clinical Resistance

Virologic failure on maraviroc can result from genotypic and phenotypic resistance to maraviroc, through outgrowth of undetected CXCR4-using virus present before maraviroc treatment (see Tropism below), through resistance to background therapy drugs (Table 11), or due to low exposure to maraviroc [see Clinical Pharmacology (12.2)].

Antiretroviral treatment-experienced subjects (Studies A4001027 and A4001028)

Week 48 data from treatment-experienced subjects failing maraviroc-containing regimens with CCR5-tropic virus (n=58) have identified 22 viruses that had decreased susceptibility to maraviroc characterized in phenotypic drug assays by concentration response curves that did not reach 100% inhibition. Additionally, CCR5-tropic virus from 2 of these treatment failure subjects had ≥3-fold shifts in EC50 values for maraviroc at the time of failure.

Fifteen of these viruses were sequenced in the gp120 encoding region and multiple amino acid substitutions with unique patterns in the heterogeneous V3 loop region were detected. Changes at either amino acid position 308 or 323 (HXB2 numbering) were seen in the V3 loop in 7 of the subjects with decreased maraviroc susceptibility. Substitutions outside the V3 loop of gp120 may also contribute to reduced susceptibility to maraviroc.

Antiretroviral treatment-naïve subjects (Study A4001026)

Treatment-naïve subjects receiving SELZENTRY had more virologic failures and more treatment emergent resistance to the background regimen drugs compared to those receiving efavirenz (Table 11).

Table 11 Development of Resistance to MVC or EFV and Background Drugs in Antiretroviral Treatment-Naïve Trial A4001026 for Patients with CCR5-tropic Virus at Screening using Enhanced Sensitivity Trofile® Assay
 | MVC | EFV
Total N in Dataset (As-Treated) | 273 | 241
Total Virologic Failures (As-Treated) | 85(31%) | 56 (23%)
Evaluable Virologic Failures with Post Baseline Genotypic and Phenotypic Data | 73 | 43
• Lamivudine Resistance | 39 (53%) | 13 (30%)
• Zidovudine Resistance | 2 (3%) | 0
• Efavirenz Resistance | -- | 23 (53%)
• Phenotypic Resistance to MVC [Includes subjects failing with CXCR4- or dual/mixed-tropism because these viruses are not intrinsically susceptible to maraviroc.] | 19 (26 %)

In an as-treated analysis of treatment-naïve subjects at 96 weeks, 32 subjects failed a maraviroc-containing regimen with CCR5-tropic virus and had a tropism result at failure; 7 of these subjects had evidence of maraviroc phenotypic resistance defined as concentration response curves that did not reach 95% inhibition. One additional subject had a ≥3-fold shift in the EC50 value for maraviroc at the time of failure. A clonal analysis of the V3 loop amino acid envelope sequences was performed from 6 of the 7 subjects. Changes in V3 loop amino acid sequence differed between each of these different subjects, even for those infected with the same virus clade suggesting that that there are multiple diverse pathways to maraviroc resistance. The subjects who failed with CCR5-tropic virus and without a detectable maraviroc shift in susceptibility were not evaluated for genotypic resistance.

Of the 32 maraviroc virologic failures failing with CCR5-tropic virus, 20(63%) also had genotypic and/or phenotypic resistance to background drugs in the regimen (lamivudine, zidovudine).

Tropism

In both treatment-experienced and treatment-naive subjects, detection of CXCR4-using virus prior to initiation of therapy has been associated with a reduced virologic response to maraviroc.

Antiretroviral treatment-experienced subjects

In the majority of cases, treatment failure on maraviroc was associated with detection of CXCR4-using virus (i.e., CXCR4-or dual/mixed-tropic) which was not detected by the tropism assay prior to treatment. CXCR4-using virus was detected at failure in approximately 55% of subjects who failed treatment on maraviroc by week 48, as compared to 9% of subjects who experienced treatment failure in the placebo arm. To investigate the likely origin of the on-treatment CXCR4-using virus, a detailed clonal analysis was conducted on virus from 20 representative subjects (16 subjects from the maraviroc arms and 4 subjects from the placebo arm) in whom CXCR4-using virus was detected at treatment failure. From analysis of amino acid sequence differences and phylogenetic data, it was determined that CXCR4-using virus in these subjects emerged from a low level of pre-existing CXCR4-using virus not detected by the tropism assay (which is population-based) prior to treatment rather than from a co-receptor switch from CCR5-tropic virus to CXCR4-using virus resulting from mutation in the virus.

Detection of CXCR4-using virus prior to initiation of therapy has been associated with a reduced virological response to maraviroc. Furthermore, subjects failing maraviroc BID at week 48 with CXCR4-using virus had a lower median increase in CD4^+ cell counts from baseline (+41 cells/mm^3) than those subjects failing with CCR5-tropic virus (+162 cells/mm^3). The median increase in CD4^+ cell count in subjects failing in the placebo arm was +7 cells/mm^3.

Antiretroviral treatment-naïve subjects

In a 96-week study of antiretroviral treatment-naïve subjects, 14% (12/85) who had CCR5-tropic virus at screening with an enhanced sensitivity tropism assay (Trofile®) and failed therapy on maraviroc had CXCR4-using virus at the time of treatment failure. A detailed clonal analysis was conducted in two previously antiretroviral treatment-naïve subjects enrolled in a Phase 2a monotherapy study who had CXCR4-using virus detected after 10 days treatment with maraviroc. Consistent with the detailed clonal analysis conducted in treatment-experienced subjects, the CXCR4-using variants appear to emerge from outgrowth of a pre-existing undetected CXCR4-using virus. Screening with an enhanced sensitivity tropism assay reduced the number of maraviroc virologic failures with CXCR4- or dual/mixed-tropic virus at failure to 12 compared to 24 when screening with the original tropism assay. All but one (11/12; 92%) of the maraviroc failures failing with CXCR4 or dual/mixed-tropic virus also had genotypic and phenotypic resistance to the background drug lamivudine at failure and 33% (4 /12) developed zidovudine-associated resistance substitutions.

Subjects who had CCR5-tropic virus at baseline and failed maraviroc therapy with CXCR4-using virus had a median increase in CD4^+ cell counts from baseline of +113 cells/mm^3 while those subjects failing with CCR5-tropic virus had an increase of +135 cells/mm^3. The median increase in CD4^+ cell count in subjects failing in the efavirenz arm was + 95 cells/mm^3.

13 NONCLINICAL TOXICOLOGY

13.1 Carcinogenesis, Mutagenesis, Impairment of Fertility

Carcinogenesis

Long-term oral carcinogenicity studies of maraviroc were carried out in rasH2 transgenic mice (6 months) and in rats for up to 96 weeks (females) and 104 weeks (males). No drug-related increases in tumor incidence were found in mice at 1500 mg/kg/day and in male and female rats at 900 mg/kg/day. The highest exposures in rats were approximately 11 times those observed in humans at the therapeutic dose of 300 mg twice daily for the treatment of HIV-1 infection.

Mutagenesis

Maraviroc was not genotoxic in the reverse mutation bacterial test (Ames test in Salmonella and E. coli), a chromosome aberration test in human lymphocytes and rat bone marrow micronucleus test.

Impairment of Fertility

Maraviroc did not impair mating or fertility of male or female rats and did not affect sperm of treated male rats at approximately 20-fold higher exposures (AUC) than in humans given the recommended 300 mg twice daily dose.

14 CLINICAL STUDIES

The clinical efficacy and safety of SELZENTRY is derived from analyses of data from three ongoing studies in adult subjects infected with CCR5-tropic HIV-1: A4001027 and A4001028, in antiretroviral treatment-experienced adult subjects and A4001026 in treatment-naïve subjects. These studies are supported by a 48-week study in antiretroviral treatment-experienced adult subjects infected with dual/mixed-tropic HIV-1, A4001029.

14.1 Studies in CCR5-tropic, Treatment-Experienced Subjects

Studies A4001027 and A4001028 are ongoing, double-blind, randomized, placebo-controlled, multicenter studies in subjects infected with CCR5-tropic HIV-1. Subjects were required to have an HIV-1 RNA of greater than 5,000 copies/mL despite at least 6 months of prior therapy with at least one agent from three of the four antiretroviral drug classes [≥1 nucleoside reverse transcriptase inhibitors (NRTI), ≥1 non-nucleoside reverse transcriptase inhibitors (NNRTI), ≥2 protease inhibitors (PI), and/or enfuvirtide] or documented resistance to at least one member of each class. All subjects received an optimized background regimen consisting of 3 to 6 antiretroviral agents (excluding low-dose ritonavir) selected on the basis of the subject's prior treatment history and baseline genotypic and phenotypic viral resistance measurements. In addition to the optimized background regimen, subjects were then randomized in a 2:2:1 ratio to maraviroc 300 mg once daily, maraviroc 300 mg twice daily, or placebo. Doses were adjusted based on background therapy as described in Dosing and Administration, Table 1.

In the pooled analysis for A4001027 and A4001028, the demographics and baseline characteristics of the treatment groups were comparable (Table 12). Of the 1043 subjects with a CCR5 tropism result at screening, 7.6% had a dual/mixed tropism result at the baseline visit 4 to 6 weeks later. This illustrates the background change from CCR5 to dual/mixed tropism result over time in this treatment-experienced population, prior to a change in antiretroviral regimen or administration of a CCR5 co-receptor antagonist.

Table 12 Demographic and Baseline Characteristics of Subjects in Studies A4001027 and A4001028
 | SELZENTRY BID N = 426 | Placebo N = 209
Age (years)
Mean (Range) | 46.3 (21–73) | 45.7 (29–72)
Sex
Male | 382 (89.7%) | 185 (88.5%)
Female | 44 (10.3%) | 24 (11.5%)
Race
White | 363 (85.2%) | 178 (85.2%)
Black | 51 (12.0%) | 26 (12.4%)
Other | 12 (2.8%) | 5 (2.4%)
Region
U.S. | 276 (64.8%) | 135 (64.6%)
Non-U.S. | 150 (35.2%) | 74 (35.4%)
Subjects with Previous Enfuvirtide Use | 142 (33.3%) | 62 (29.7)
Subjects with Enfuvirtide as Part of OBT | 182 (42.7%) | 91 (43.5%)
Baseline Plasma HIV-1 RNA (log10 copies/mL)
Mean (Range) | 4.85 (2.96–6.88) | 4.86 (3.46–7.07)
Subjects with Screening Viral Load ≥100,000 copies/mL | 179 (42.0%) | 84 (40.2%)
Baseline CD4+ Cell Count (cells/mm^3)
Median (Range) | 167 (2–820) | 171 (1–675)
Subjects with Baseline CD4+ Cell Count ≤200 cells/mm^3) | 250 (58.7%) | 118 (56.5%)
Subjects with Overall Susceptibility Score (OSS): [OSS -Sum of active drugs in OBT based on combined information from genotypic and phenotypic testing.]
0 | 57 (13.4%) | 35 (16.7%)
1 | 136 (31.9%) | 44 (21.1%)
2 | 104 (24.4%) | 59 (28.2%)
≥3 | 125 (29.3%) | 66 (31.6%)
Subjects with enfuvirtide resistance mutations | 90 (21.2%) | 45 (21.5%)
Median Number of Resistance-Associated: [Resistance mutations based on IAS guidelines^1]
PI mutations | 10 | 10
NNRTI mutations | 1 | 1
NRTI mutations | 6 | 6

The week 48 results for the pooled Studies A4001027 and A4001028 are shown in Table 13.

Table 13 Outcomes of Randomized Treatment at Week 48 Studies A4001027 and A4001028
Outcome | SELZENTRY BID N=426 | PLACEBO N=209 | Mean Difference
Mean change from Baseline to Week 48 in HIV-1 RNA (log10 copies/mL) | -1.84 | -0.78 | -1.05
<400 copies/mL at Week 48 | 239 (56%) | 47 (22%) | 34%
<50 copies/mL at Week 48 | 194 (46%) | 35 (17%) | 29%
Discontinuations
Insufficient Clinical Response | 97 (23%) | 113 (54%)
Adverse Events | 19 (4%) | 11 (5%)
Other | 27 (6%) | 18 (9%)
Subjects with treatment-emergent CDC Category C events | 22 (5%) | 16 (8%)
Deaths (during study or within 28 days of last dose) | 9 (2%) [One additional subject died while receiving open-label maraviroc therapy subsequent to discontinuing double-blind placebo due to insufficient response] | 1 (0.5%)

After 48 weeks of therapy, the proportion of subjects with HIV-1 RNA <400 copies/mL receiving maraviroc compared to placebo was 56% and 22%, respectively. The mean changes in plasma HIV-1 RNA from baseline to week 48 were –1.84 log10 copies/mL for subjects receiving maraviroc + OBT compared to –0.78 log10 copies/mL for subjects receiving OBT only. The mean increase in CD4+ counts was higher on maraviroc twice daily + OBT (124 cells/mm^3) than on placebo + OBT (60 cells/mm^3).

14.2 Study in Dual/Mixed-tropic, Treatment-Experienced Subjects

Study A4001029 was an exploratory, randomized, double-blind, multicenter trial to determine the safety and efficacy of maraviroc in subjects infected with dual/mixed co-receptor tropic HIV-1. The inclusion/exclusion criteria were similar to those for Studies A4001027 and A4001028 above and the subjects were randomized in a 1:1:1 ratio to SELZENTRY once daily, SELZENTRY twice daily, or placebo. No increased risk of infection or HIV disease progression was observed in the subjects who received SELZENTRY. SELZENTRY use was not associated with a significant decrease in HIV-1 RNA compared to placebo in these subjects and no adverse effect on CD4 count was noted.

14.3 Study in Treatment-Naïve Subjects

Study A4001026 is an ongoing, randomized, double-blind, multicenter study in subjects infected with CCR5-tropic HIV-1 classified by the original Trofile® tropism assay. Subjects were required to have plasma HIV-1 RNA ≥2000 copies/mL and could not have: 1) previously received any antiretroviral therapy for >14 days, 2) an active or recent opportunistic infection or a suspected primary HIV-1 infection, or 3) phenotypic or genotypic resistance to zidovudine, lamivudine, or efavirenz. Subjects were randomized in a 1:1:1 ratio to maraviroc 300 mg once daily, maraviroc 300 mg twice daily, or efavirenz 600 mg once daily, each in combination with zidovudine/lamivudine. The efficacy and safety of SELZENTRY are based on the comparison of SELZENTRY twice daily versus efavirenz. In a pre-planned interim analysis at 16 weeks, the maraviroc 300mg once per day treatment arm failed to meet the pre-specified criteria for demonstrating non-inferiority and was discontinued.

The demographic and baseline characteristics of the maraviroc and efavirenz treatment groups were comparable (Table 14). Subjects were stratified by screening HIV-1 RNA levels and by geographic region. The median CD4 cell counts and mean HIV-1 RNA at baseline were similar for both treatment groups.

Table 14 Demographic and Baseline Characteristics of Subjects in Study A4001026
 | SELZENTRY 300 mg BID + zidovudine/lamivudine (N=360) | Efavirenz 600 mg QD + zidovudine/lamivudine (N=361)
Age (years)
Mean | 36.7 | 37.4
Range | 20–69 | 18–77
Female n (%) | 104 (29) | 102 (28)
Race, n (%)
White | 204 (57) | 198 (55)
Black | 123 (34) | 133 (37)
Asian | 6 (2) | 5 (1)
Other | 27 (8) | 25 (7)
Median (Range) CD4 cell count (cells/µL) | 241 (5–1422) | 254 (8–1053)
Median (Range) HIV-1 RNA (log 10 copies/mL) | 4.9 (3 –7) | 4.9 (3 –7)

The treatment outcomes at 96 weeks for study A4001026 are shown in Table 15. Treatment outcomes are based on reanalysis of the screening samples using a more sensitive tropism assay, Enhanced sensitivity Trofile® HIV tropism assay, which became available after the week 48 analysis, approximately 15% of the subjects identified as CCR5-tropic in the original analysis had Dual/Mixed- or CXCR4-tropic virus. Screening with enhanced sensitivity version of the Trofile® tropism assay reduced the number of maraviroc virologic failures with CXCR4- or Dual/Mixed-tropic virus at failure to 12 compared to 24 when screening with the original Trofile® HIV tropism assay.

Table 15: Study Outcome (Snapshot) at Week 96 Using Enhanced Sensitivity Assay [The total number of subjects (Ns) in Table 15 represents the subjects who had a CCR5-tropic virus in the reanalysis of screening samples using the more sensitive tropism assay. This reanalysis reclassified approximately 15% of subjects shown in Table 14 as having Dual/Mixed- or CXCR4-tropic virus. These numbers are different than those presented in table 14 because the numbers in Table 14 reflect the subjects with CCR5-tropic virus according to the original tropism assay.]
Outcome at week 96 [Week 48 results: Virologic responders (<400): 228/311 (73%) in SELZENTRY, 219/303 (72%) in Efavirenz Virologic responders (<50): 213/311 (69 %) in SELZENTRY, 207/303 (68%) in Efavirenz] | SELZENTRY 300 mg BID + zidovudine/lamivudine N = 311 n (%) | Efavirenz 600 mg QD +zidovudine/lamivudine N = 303 n (%)
Virologic Responders: (HIV-1 RNA <400 copies/mL) | 199 (64) | 195 (64)
Virologic Failure:
• Non-sustained HIV-1 RNA Suppression | 39 (13) | 22 (7)
• HIV-1 RNA Never Suppressed | 9(3) | 1(<1)
Virologic Responders: (HIV-1 RNA <50 copies/mL) | 183 (59) | 190 (63)
Virologic Failure:
• Non-sustained HIV-1 RNA Suppression | 43 (14) | 25 (8)
• HIV-1 RNA Never Suppressed | 21 (7) | 3 (1)
Discontinuations due to:
• Adverse Events | 19 (6) | 47 (16)
• Death | 2 (1) | 2 (1)
Other [Other reasons for discontinuation include lost to follow-up, withdrawn, protocol violation, and other.] | 43 (14) | 36 (12)

The median increase from baseline in CD4+ cell counts at week 96 was 184 cells/mm^3 for the SELZENTRY arm compared to 155 cells/mm3 for the efavirenz arm.

15 REFERENCES

^1 IAS-USA Drug Resistance Mutations Figures http://www.iasusa.org/pub/topics/2006/issue3/125.pdf

16 HOW SUPPLIED/STORAGE AND HANDLING

SELZENTRY film-coated tablets are available as follows:

300 mg tablets are blue, biconvex, oval, film-coated tablets debossed with "Pfizer" on one side and "MVC 300" on the other.

Bottle packs 300 mg tablets

- 60 tablets (NDC 54868-5809-0)

STORAGE AND HANDLING

SELZENTRY film-coated tablets should be stored at 25°C (77°F); excursions permitted between 15°C and 30°C (59°F–86°F) [see USP Controlled Room Temperature].

Shelf life is 24 months.

17 PATIENT COUNSELING INFORMATION

See Medication Guide.

Patients should be informed that if they develop signs or symptoms of hepatitis or allergic reaction following use of SELZENTRY (rash, skin or eyes look yellow, dark urine, vomiting, abdominal pain), they should stop SELZENTRY and seek medical evaluation immediately [see Warnings and Precautions (5.1)].

Patients should be informed that SELZENTRY is not a cure for HIV infection and patients may still develop illnesses associated with HIV infection, including opportunistic infections. The use of SELZENTRY has not been shown to reduce the risk of transmission of HIV to others through sexual contact, sharing needles or blood contamination.

Patients should be advised that it is important to:

- remain under the care of a physician when using SELZENTRY;
- take SELZENTRY every day as prescribed and in combination with other antiretroviral drugs;
- report to their physician the use of any other prescription or nonprescription medication or herbal products;
- inform their physician if they are pregnant, plan to become pregnant or become pregnant while taking SELZENTRY;
- not change the dose or dosing schedule of SELZENTRY or any antiretroviral medication without consulting their physician.

Patients should be advised that it is important to take all their anti-HIV medicines as prescribed and at the same time(s) each day.

Patients should be advised that when their SELZENTRY supply starts to run low, they should ask their doctor or pharmacist for a refill.

Patients should be advised that if they forget to take a dose, they should take the next dose of SELZENTRY as soon as possible and then take their next scheduled dose at its regular time. If it is less than 6 hours before their next scheduled dose, they should not take the missed dose and should instead wait and take the next dose at the regular time.

Caution should be used when administering SELZENTRY in patients with a history of postural hypotension or on concomitant medication known to lower blood pressure. Patients should be advised that if they experience dizziness while taking SELZENTRY, they should avoid driving or operating machinery.

Trofile® is a registered trademark of Monogram Biosciences, Inc.

LAB-0357-5.0

Additional barcode labeling by:
Physicians Total Care, Inc.
Tulsa, Oklahoma 74146

MEDICATION GUIDE

SELZENTRY® (sell-ZEN-tree) Tablets
(maraviroc)

Read the Medication Guide that comes with SELZENTRY before you start taking it and each time you get a refill. There may be new information. This information does not take the place of talking with your health care provider about your medical condition or treatment.

What is the most important information I should know about SELZENTRY?

Serious side effects have occurred with SELZENTRY, including liver problems (liver toxicity). An allergic reaction may happen before liver problems occur. Stop taking SELZENTRY and call your health care provider right away if you get any of the following symptoms:

- an itchy rash on your body (allergic reaction)
- yellowing of your skin or whites of your eyes (jaundice)
- dark (tea-colored) urine
- vomiting
- upper right stomach area (abdominal) pain

What is SELZENTRY?

SELZENTRY is an anti-HIV medicine called a CCR5 antagonist. HIV (Human Immunodeficiency Virus) is the virus that causes AIDS (Acquired Immune Deficiency Syndrome).

SELZENTRY is used with other anti-HIV medicines in adults with CCR5-tropic HIV-1 infection.

Use of SELZENTRY is not recommended in people with dual/mixed or CXCR4-tropic HIV-1.

- SELZENTRY will not cure HIV infection.
- People taking SELZENTRY may still develop infections, including opportunistic infections or other conditions that happen with HIV infection.
- It is very important that you stay under the care of your health care provider during treatment with SELZENTRY.
- The long-term effects of SELZENTRY are not known at this time.

SELZENTRY has not been studied in children less than 16 years of age.

Does SELZENTRY lower the risk of passing HIV to other people?

No, SELZENTRY does not lower the risk of passing HIV to other people through sexual contact, sharing needles, or being exposed to your blood.

- Continue to practice safer sex.
- Use latex or polyurethane condoms or other barrier methods to lower the chance of sexual contact with any body fluids. This includes semen from a man, vaginal secretions from a woman, or blood.
- Never re-use or share needles.
- Ask your health care provider if you have any questions about safer sex or how to prevent passing HIV to other people.

How does SELZENTRY work?

HIV enters cells in your blood by attaching itself to structures on the surface of the cell called receptors. SELZENTRY blocks a specific receptor called CCR5 that CCR5-tropic HIV-1 uses to enter CD4 or T-cells in your blood. Your health care provider will do a blood test to see if you have been infected with CCR5-tropic HIV-1 before prescribing SELZENTRY for you.

- When used with other anti-HIV medicines, SELZENTRY may:
  - reduce the amount of HIV in your blood. This is called "viral load".
  - increase the number of white blood cells called T (CD4) cells.

SELZENTRY does not work in all people with CCR5-tropic HIV-1 infection.

Who should not take SELZENTRY?

People with severe kidney problems or who are on hemodialysis and are taking certain other medications should not take SELZENTRY. Talk to your healthcare provider before taking this medicine if you have kidney problems.

What should I tell my health care provider before taking SELZENTRY?

Before you take SELZENTRY, tell your health care provider if you:

- have liver problems including a history of hepatitis B or C.
- have heart problems.
- have kidney problems.
- have low blood pressure or take medicines to lower blood pressure.
- have any other medical condition.
- are pregnant or plan to become pregnant. It is not known if SELZENTRY may harm your unborn baby.
  Antiretroviral Pregnancy Registry. There is a pregnancy registry for women who take antiviral medicines during pregnancy. The purpose of the registry is to collect information about the health of you and your baby. Talk to your health care provider about how you can take part in this registry.
- are breastfeeding or plan to breastfeed. It is recommended that HIV-positive women should not breastfeed their babies. This is because of the chance of passing HIV to your baby. You should not breastfeed if you are taking SELZENTRY because the risk to your baby is unknown. Talk with your health care provider about the best way to feed your baby.

Tell your health care provider about all the medicines you take, including prescription and non-prescription medicines, vitamins and herbal supplements. Certain other medicines may affect the levels of SELZENTRY in your blood. Your health care provider may need to change your dose of SELZENTRY when you take it with certain medicines.

The levels of SELZENTRY in your blood may change and your health care provider may need to adjust your dose of SELZENTRY when taking any of the following medications together with SELZENTRY:

- darunavir (Prezista®)
- lopinavir/ritonavir (Kaletra®, Norvir®)
- atazanavir (Reyataz®)
- saquinavir (Invirase®)
- nelfinavir (Viracept®)
- indinavir (Crixivan®)
- fosamprenavir (Lexiva®)
- etravirine (Intelence®)
- carbamezepine (Tegretol®)
- phenytoin (Dilantin®)
- Ritonavir (Norvir®)

- delavirdine (Rescriptor®)
- ketoconazole (Nizoral®)
- itraconazole (Sporanox®)
- clarithromycin (Biaxin®)
- nefazodone (Serzone®)
- telithromycin (Ketek®)
- efavirenz (Sustiva®, Atripla®)
- rifampin (Rifadin®, Rifater®)
- phenobarbital (Luminal®)

Do not take products that contain St. John's Wort (hypericum perforatum). St. John's Wort may lower the levels of SELZENTRY in your blood so that it will not work to treat your CCR5-tropic HIV infection.

Know the medicines you take. Keep a list of your medicines. Show the list to your health care provider and pharmacist when you get a new medicine.

How should I take SELZENTRY?

Take SELZENTRY exactly as prescribed by your health care provider. SELZENTRY comes in 150 mg and 300 mg tablets. Your health care provider will prescribe the dose that is right for you.

- Take SELZENTRY 2 times a day.
- Swallow SELZENTRY tablets whole. Do not chew the tablets.
- Take SELZENTRY tablets with or without food.
- Always take SELZENTRY with other anti-HIV drugs as prescribed by your health care provider.

Do not change your dose or stop taking SELZENTRY or your other anti-HIV medicines without first talking with your health care provider.

- If you take too much SELZENTRY, call your health care provider or the poison control center right away.
- If you forget to take SELZENTRY, take the next dose of SELZENTRY as soon as possible and then take your next scheduled dose at its regular time. If it is less than 6 hours before your next dose, do not take the missed dose. Wait and take the next dose at the regular time. Do not take a double dose to make up for a missed dose.
- It is very important to take all your anti-HIV medicines as prescribed. This can help your medicines work better. It also lowers the chance that your medicines will stop working to fight HIV (drug resistance).
- When your SELZENTRY supply starts to run low, ask your health care provider or pharmacist for a refill. This is very important because the amount of virus in your blood may increase and SELZENTRY could stop working if it is stopped for even a short period of time.

What are the possible side effects of SELZENTRY?

There have been serious side effects when SELZENTRY has been given with other anti-HIV drugs including:

- Liver problems. See "What is the most important information I should know about SELZENTRY?"
- Heart problems including heart attack.
- Low blood pressure when standing up (postural hypotension). Low blood pressure when standing up can cause dizziness or fainting. Do not drive a car or operate heavy machinery if you have dizziness while taking SELZENTRY.
- Changes in your immune system. A condition called Immune Reconstitution Syndrome can happen when you start taking HIV medicines. Your immune system may get stronger and could begin to fight infections that have been hidden in your body such as pneumonia, herpes virus or tuberculosis. Tell your health care provider if you develop new symptoms after starting your HIV medicines.
- Possible chance of infection or cancer. SELZENTRY affects other immune system cells and therefore may possibly increase your chance for getting other infections or cancer.

The most common side effects of SELZENTRY include colds, cough, fever, rash, and dizziness.

Tell your health care provider about any side effect that bothers you or does not go away.

These are not all of the side effects with SELZENTRY. For more information, ask your health care provider or pharmacist.

Call your doctor for medical advice about side effects. You may report side effects to FDA at 1-800-FDA-1088.

How should I store SELZENTRY?

- Store SELZENTRY tablets at room temperature from 59°F to 86°F (15°C to 30°C).
- Safely throw away medicine that is out of date or that you no longer need.

Keep SELZENTRY and all medicines out of the reach of children.

General information about SELZENTRY

Medicines are sometimes prescribed for conditions that are not mentioned in Medication Guides. Do not use SELZENTRY for a condition for which it was not prescribed. Do not give SELZENTRY to other people, even if they have the same symptoms you have. It may harm them.

This Medication Guide summarizes the most important information about SELZENTRY. If you would like more information, talk with your health care provider. You can ask your health care provider or pharmacist for more information about SELZENTRY that is written for health professionals. For more information, go to www.selzentry.com.

What are the ingredients in SELZENTRY?

Active ingredient: maraviroc

Inactive ingredients: microcrystalline cellulose, dibasic calcium phosphate (anhydrous), sodium starch glycolate, magnesium stearate
Film-coat: FD&C blue #2 aluminum lake, soya lecithin, polyethylene glycol (macrogol 3350), polyvinyl alcohol, talc and titanium dioxide

The brands listed are the trademarks or registered marks of their respective owners and are not trademarks of Pfizer.

This Medication Guide has been approved by the US Food and Drug Administration.

LAB-0358-5.0
May 2010

PRINCIPAL DISPLAY PANEL - 300 mg Tablet Bottle Label

NDC 54868-5809-0

Rx only
60 Tablets

Selzentry™
(maraviroc) tablets

300 mg